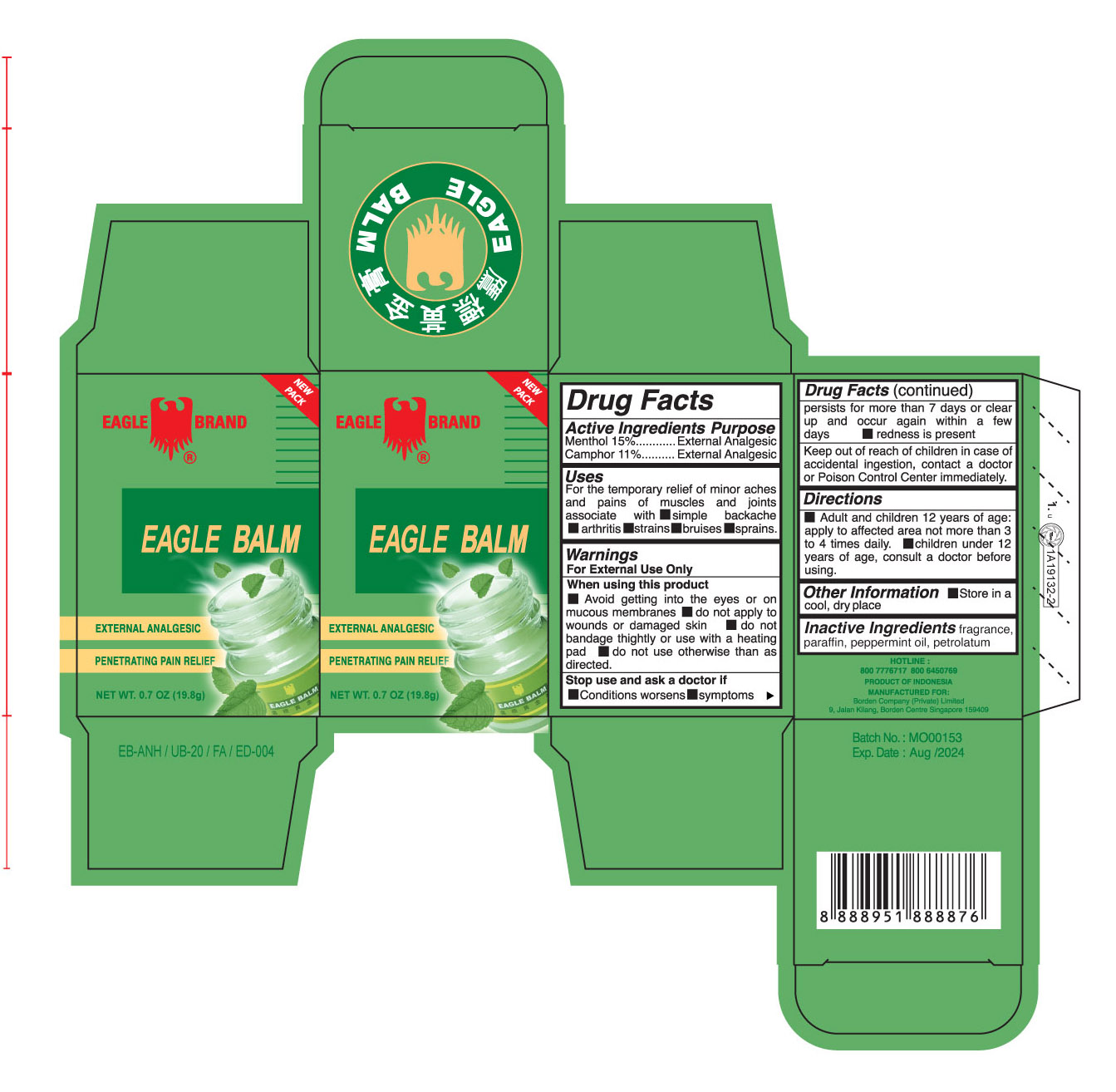 DRUG LABEL: Eagle Green Balm
NDC: 43405-100 | Form: OINTMENT
Manufacturer: Borden Company (Private) Limited
Category: otc | Type: HUMAN OTC DRUG LABEL
Date: 20241104

ACTIVE INGREDIENTS: CAMPHOR (SYNTHETIC) 11 g/100 g; MENTHOL 15 g/100 g
INACTIVE INGREDIENTS: PEPPERMINT OIL; PARAFFIN; PETROLATUM

Eagle Balm Borden

Active Ingredients

Menthol 15%

Camphor 11%

Purpose

External Analgesic

External Analgesic

Uses

For the temporary relief of minor pains and aches of muscles and joints associated with ■ simple backache ■arthritis ■strains ■bruises ■sprains

Warnings

For External Use Only

When using this product

■ Avoid getting into the eyes or on mucous membranes ■ do not apply to wounds and damaged skin ■ do not bandage tightly or use with a heating pad ■ do not use otherwise than as directed

Stop use and ask a doctor if

■ Condition worsens, ■ symptoms persist for more than 7 days or clear up and occur again within a few days ■ redness is present

Keep out of reach of children in case of accidental ingestion contact a doctor or Poison Control Center immediately

Directions

■ Adults and children 12 years of age: apply to affected area not more than 3 - 4 times daily. ■ children under 12 years of age, consult a doctor before use

Directions

Section 8 changed to reflect change in children's age for usage (from 2 years of age to 12 years of age) (July 2021)

Other Information

■ Store in a cool dry place

Inactive Ingredients

fragrance, paraffin, peppermint oil, petrolatum